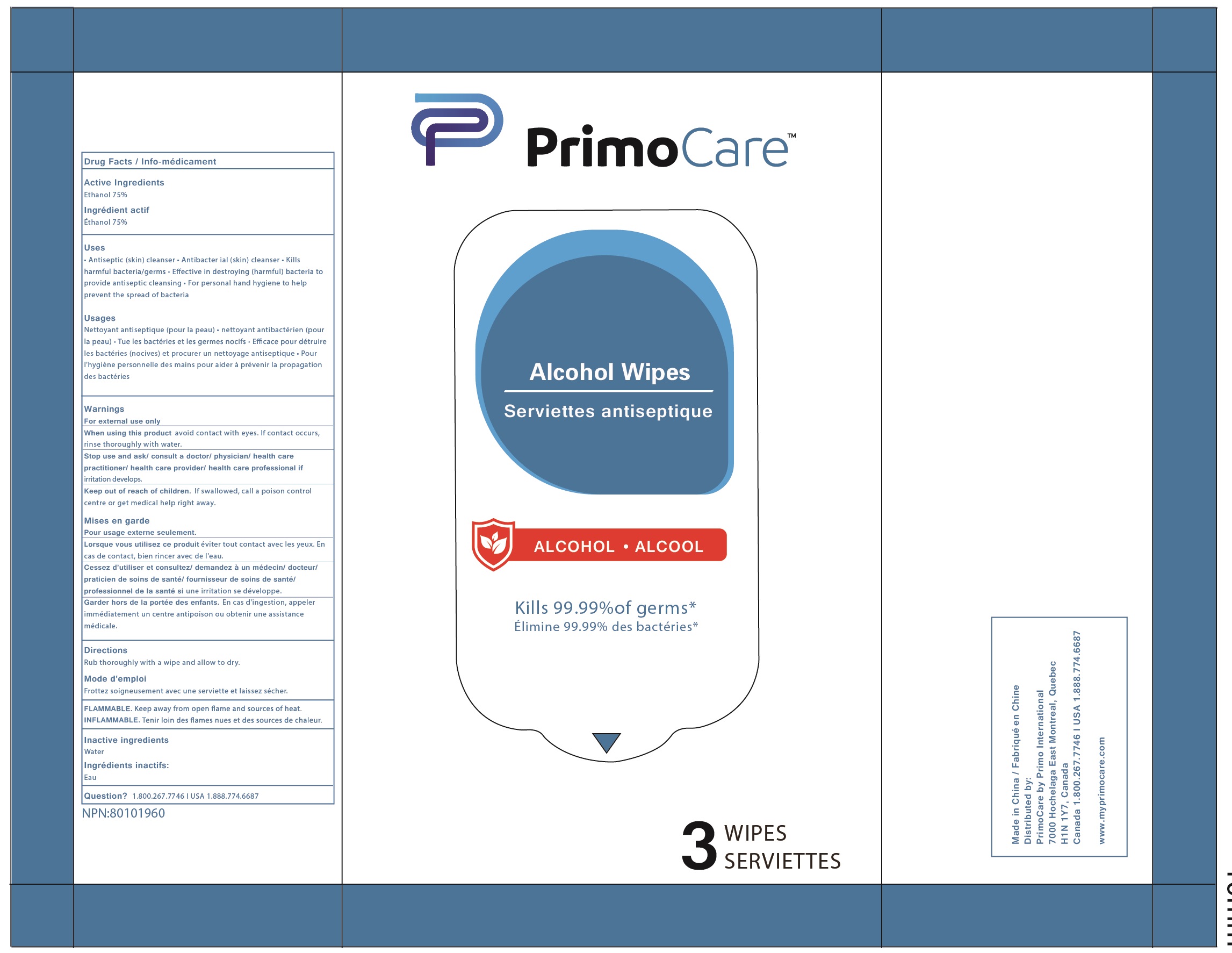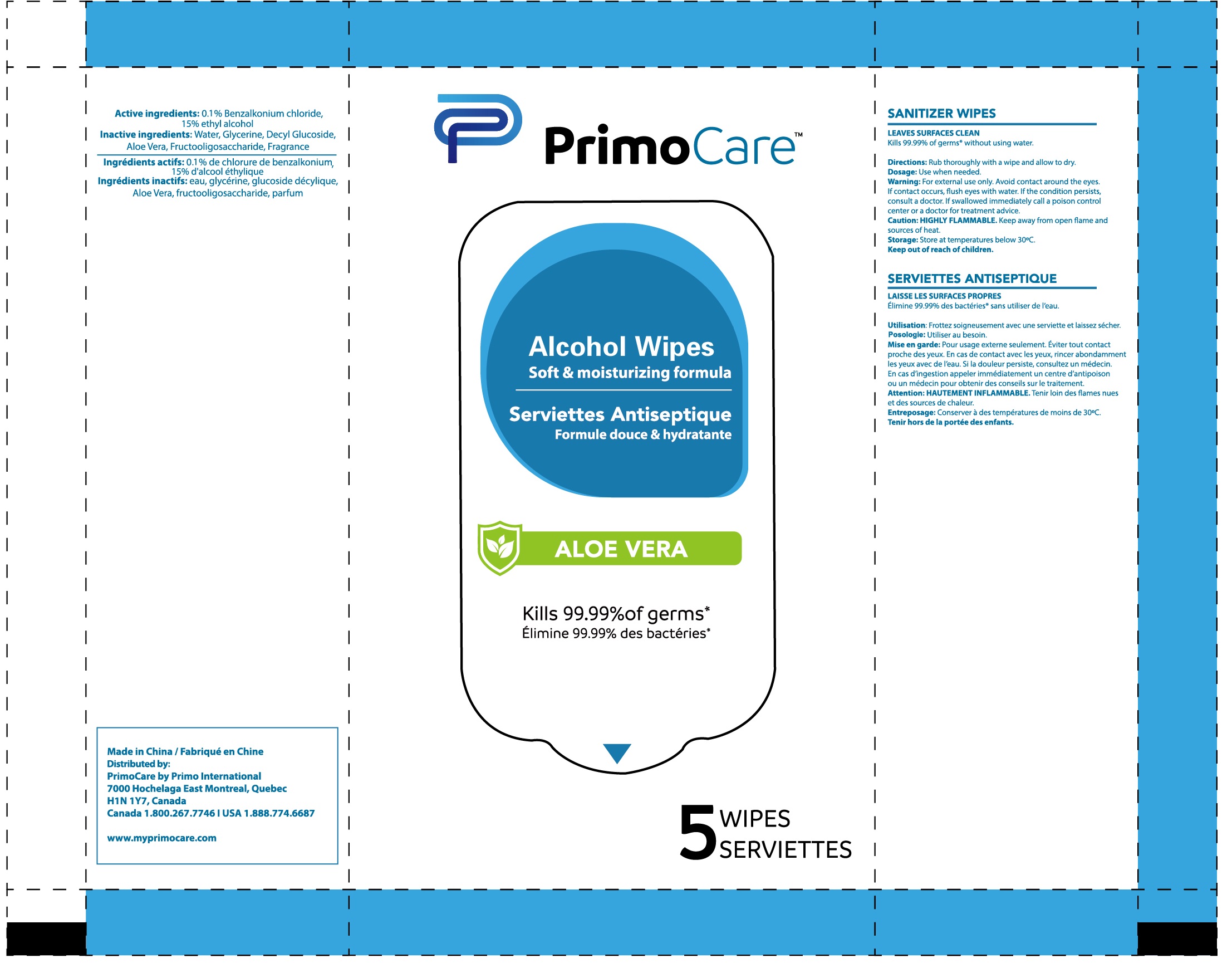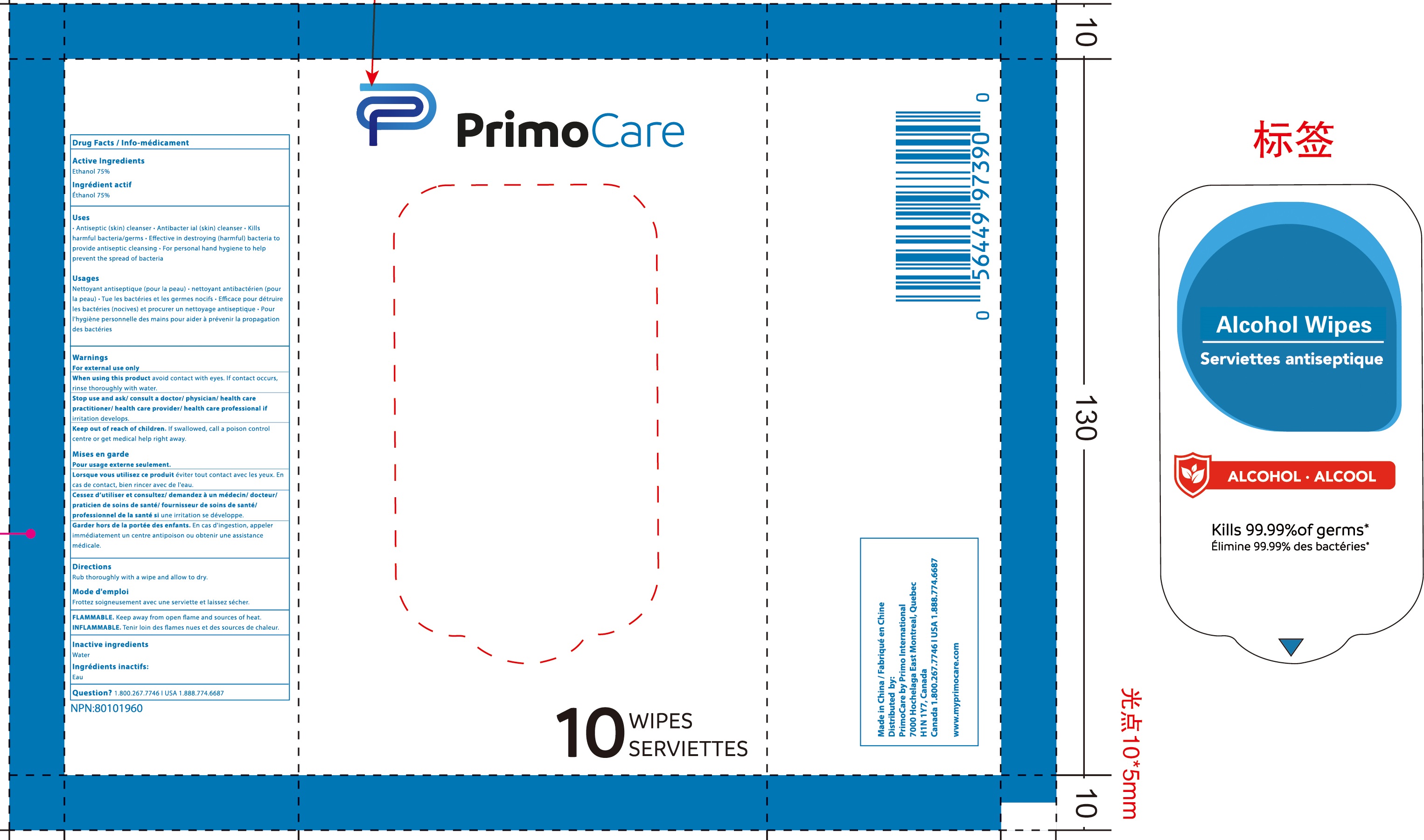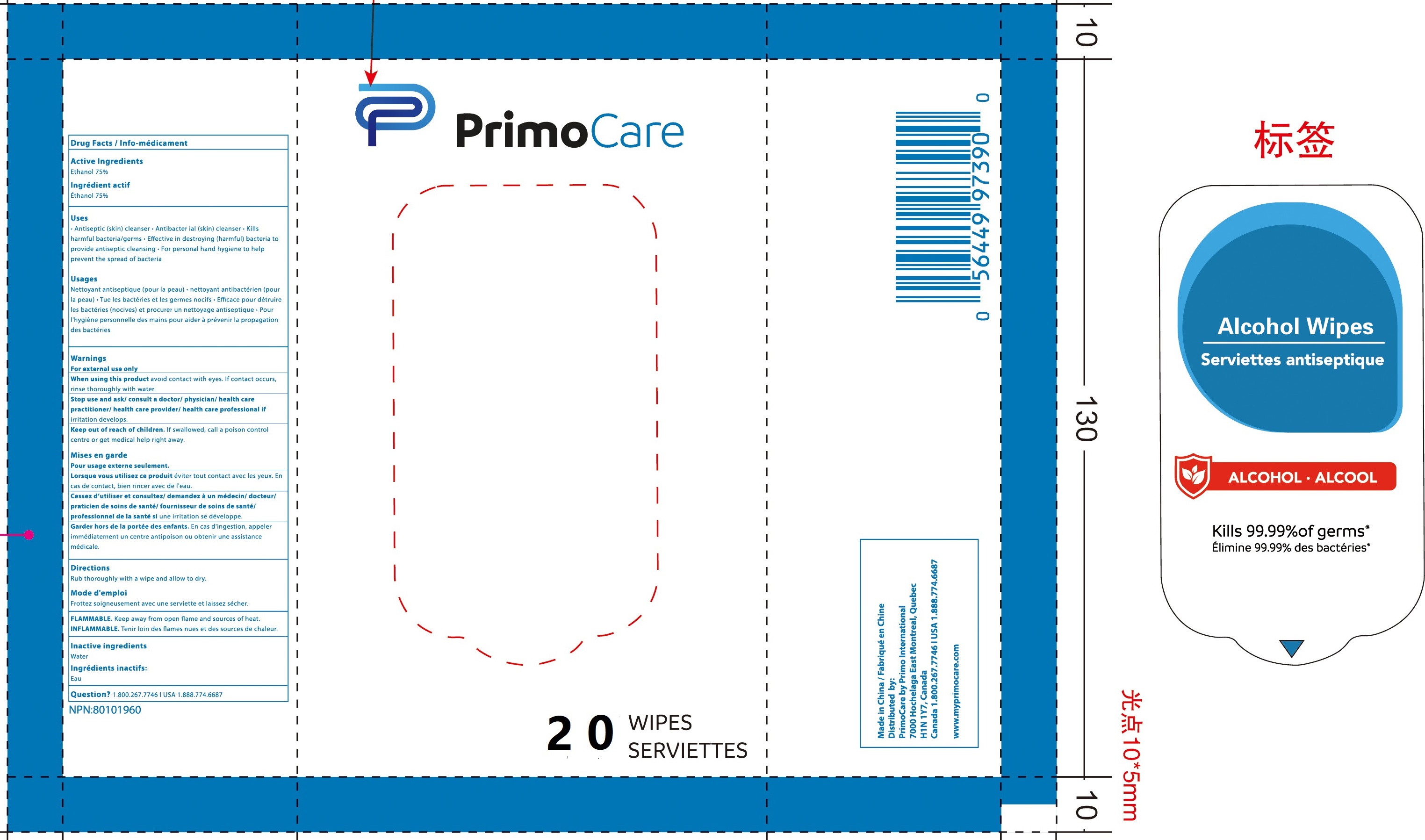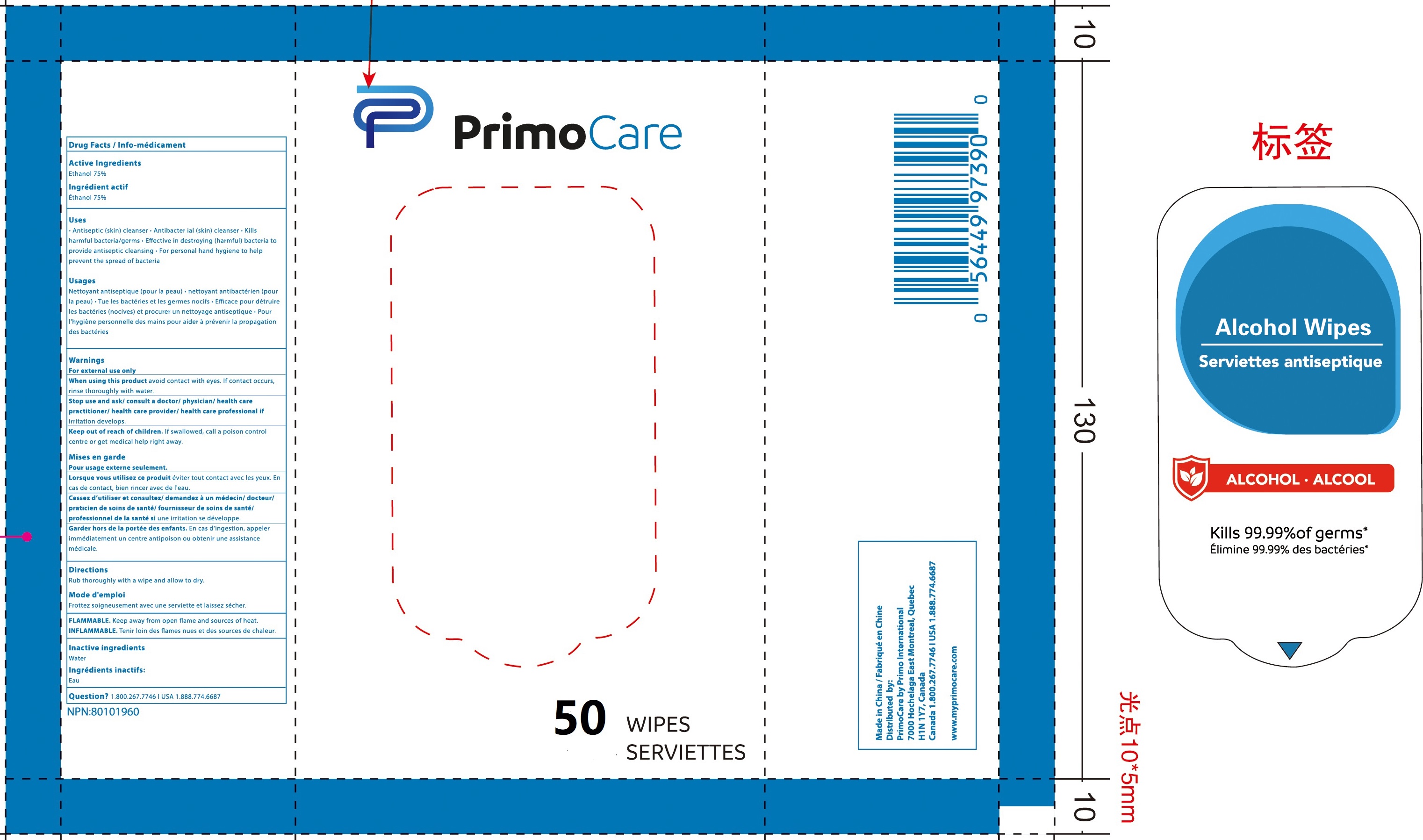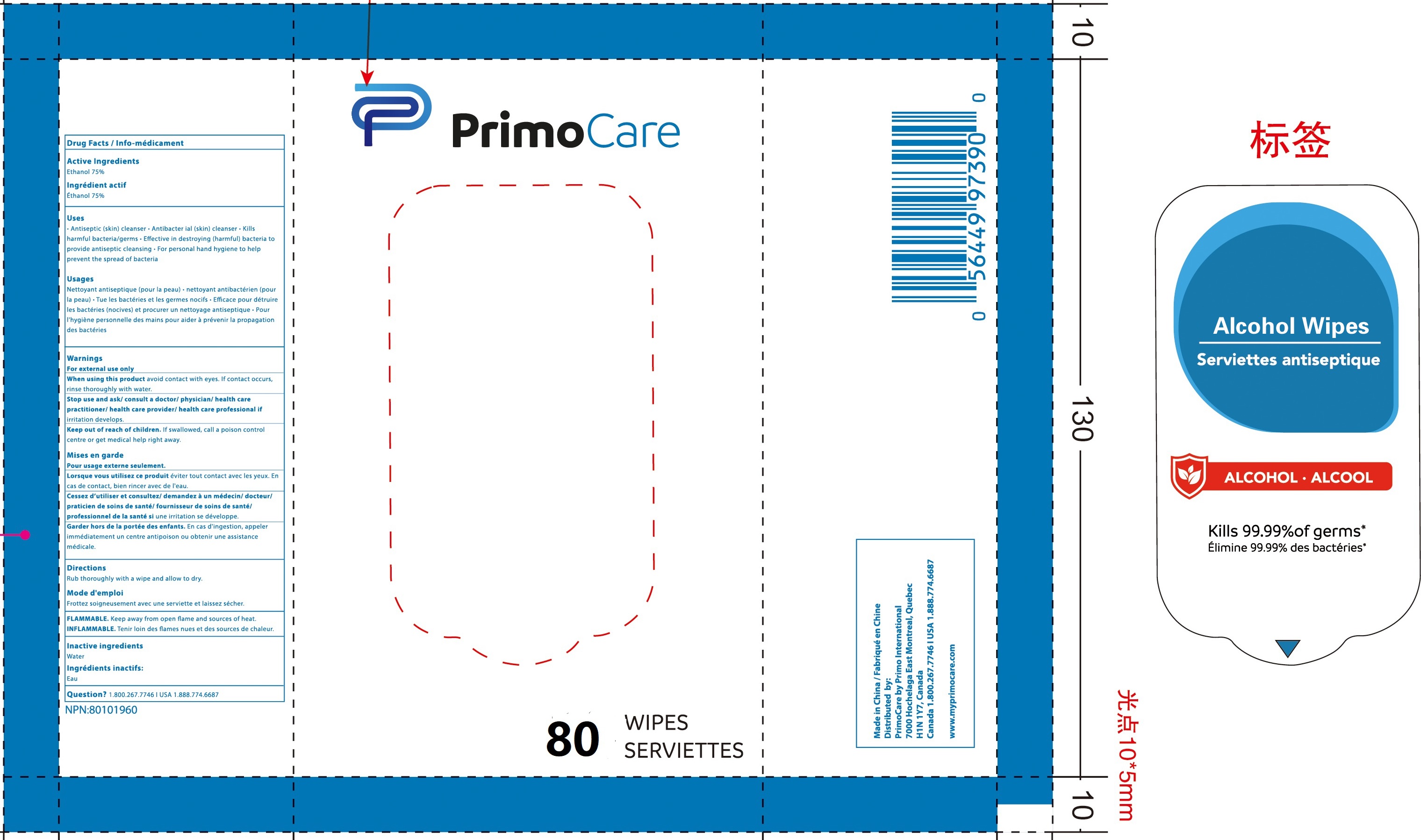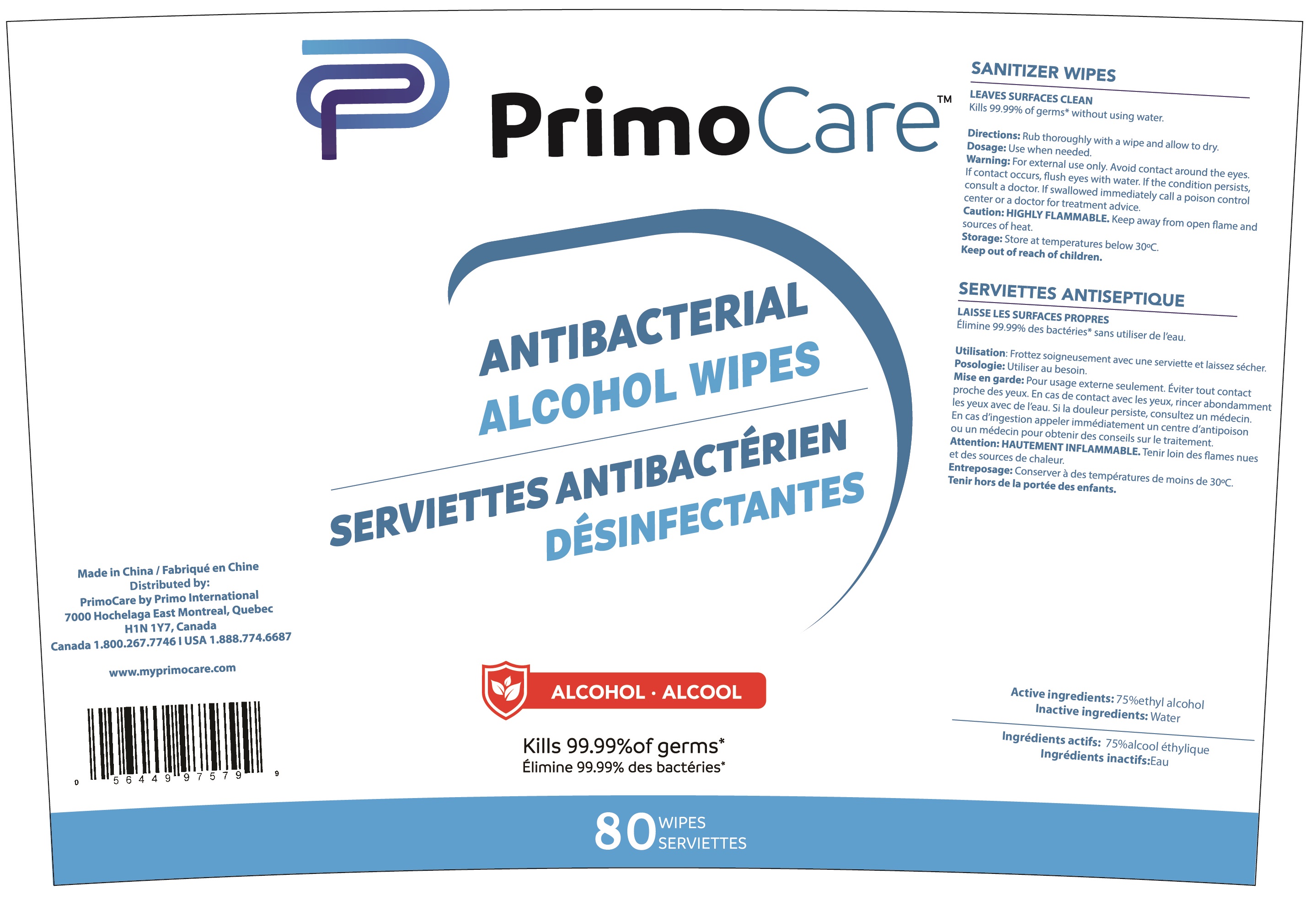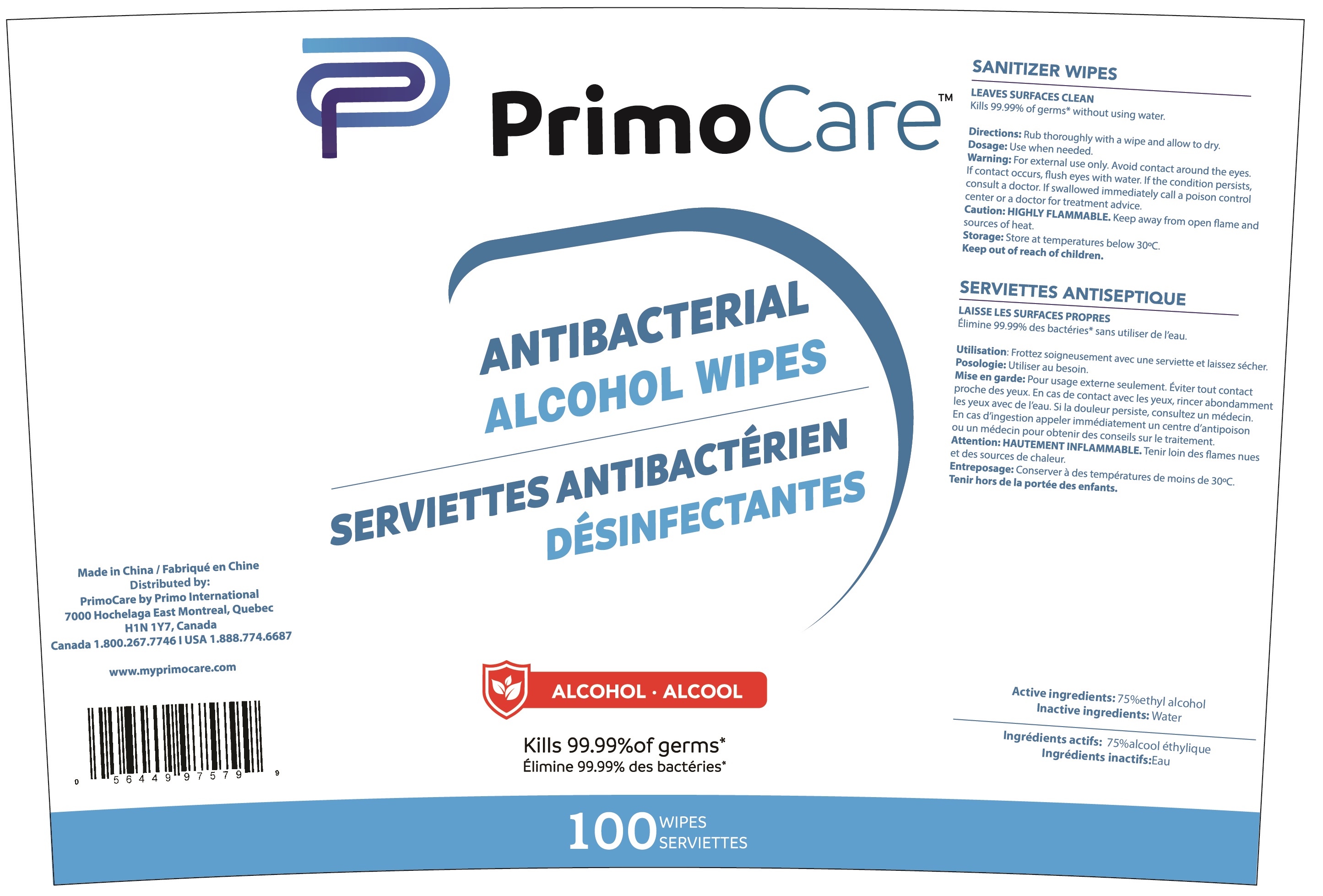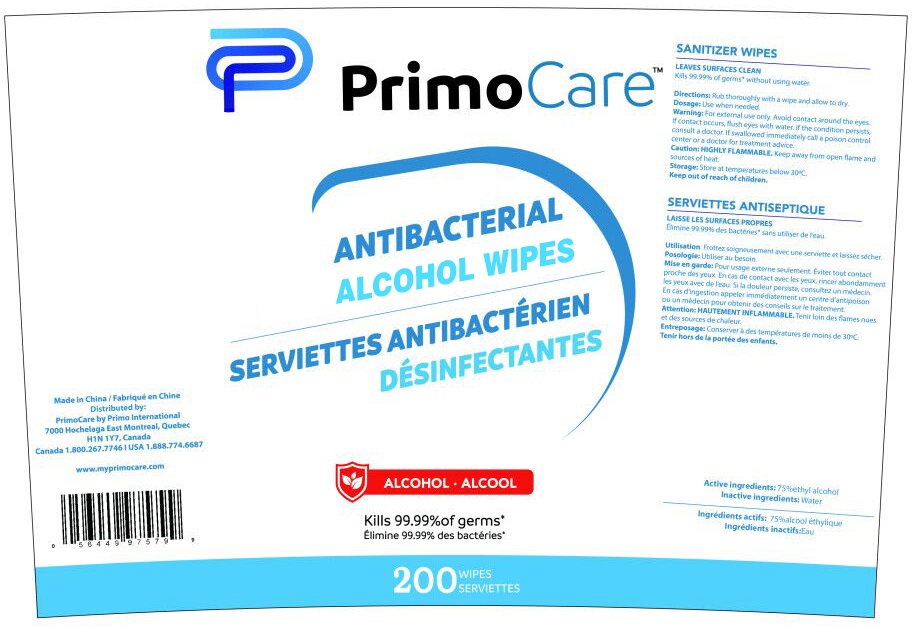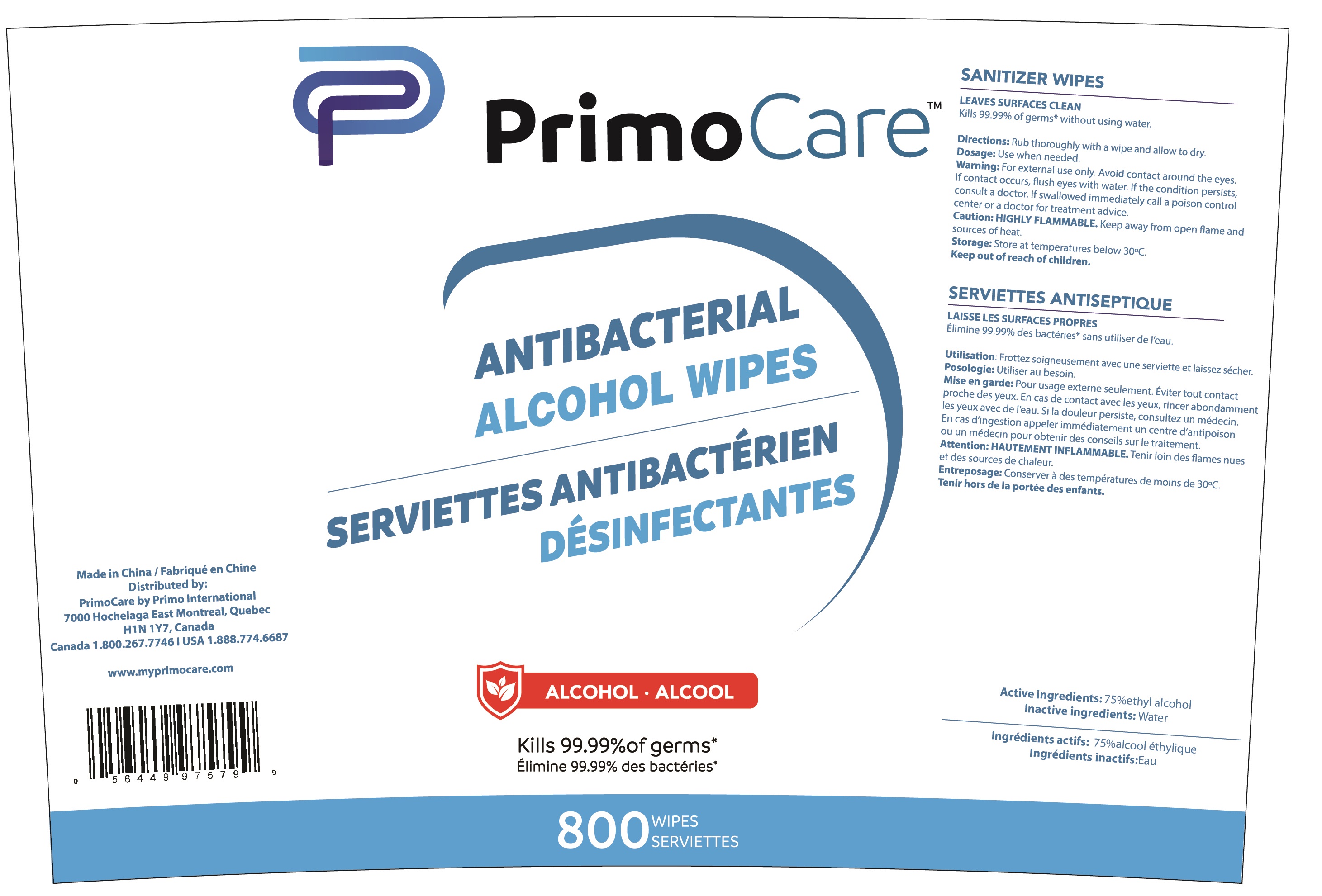 DRUG LABEL: Alcohol Wipes
NDC: 81390-002 | Form: CLOTH
Manufacturer: Ningbo Longco Commodity Co., LTD
Category: otc | Type: HUMAN OTC DRUG LABEL
Date: 20210125

ACTIVE INGREDIENTS: ALCOHOL 75 mL/100 1
INACTIVE INGREDIENTS: WATER

81390-002
Alcohol Wipes

Active Ingredient(s)

Active ingredients: 75%ethyl alcohol

Purpose

LEAVES SURFACES CLEAN

Use

LEAVES SURFACES CLEAN
Kills 99.99% of germs* without using water.

Warnings

For external use only. Avoid contact around the eyes.
If contact occurs, flush eyes with water.
If the condition persists, consult a doctor If swallowed immediately call a poison control center or a doctor for treatment advice.

Do not use

If contact occurs, flush eyes with water.

WHEN USING

Caution: HIGHLY FLAMMABLE. Keep away from open flame and sources of heat
If contact occurs, flush eyes with water.
If the condition persists, consult a doctor If swallowed immediately call a poison control center or a doctor for treatment advice.

STOP USE

If the condition persists, consult a doctor If swallowed immediately call a poison control center or a doctor for treatment advice.

Keep out of reach of children.Keep out of reach of children.

Directions

Rub thoroughly with a wipe and allow to dry.
Use when needed.

Other information

Storage: Storage: Store at temperatures below 30°C.

Inactive ingredients

Inactive ingredients: Water

Package Label - Principal Display Panel

81390-002-00 3 IN 1BAG

81390-002-01 5 IN 1BAG

81390-002-02 10 IN 1BAG

81390-002-03 20 IN 1BAG

81390-002-04 50 IN 1BAG

81390-002-05 80 IN 1BAG

81390-002-06 80 in 1DRUM

81390-002-07 100 in 1DRUM

81390-002-08 200 in 1DRUM

81390-002-09 800 in 1DRUM